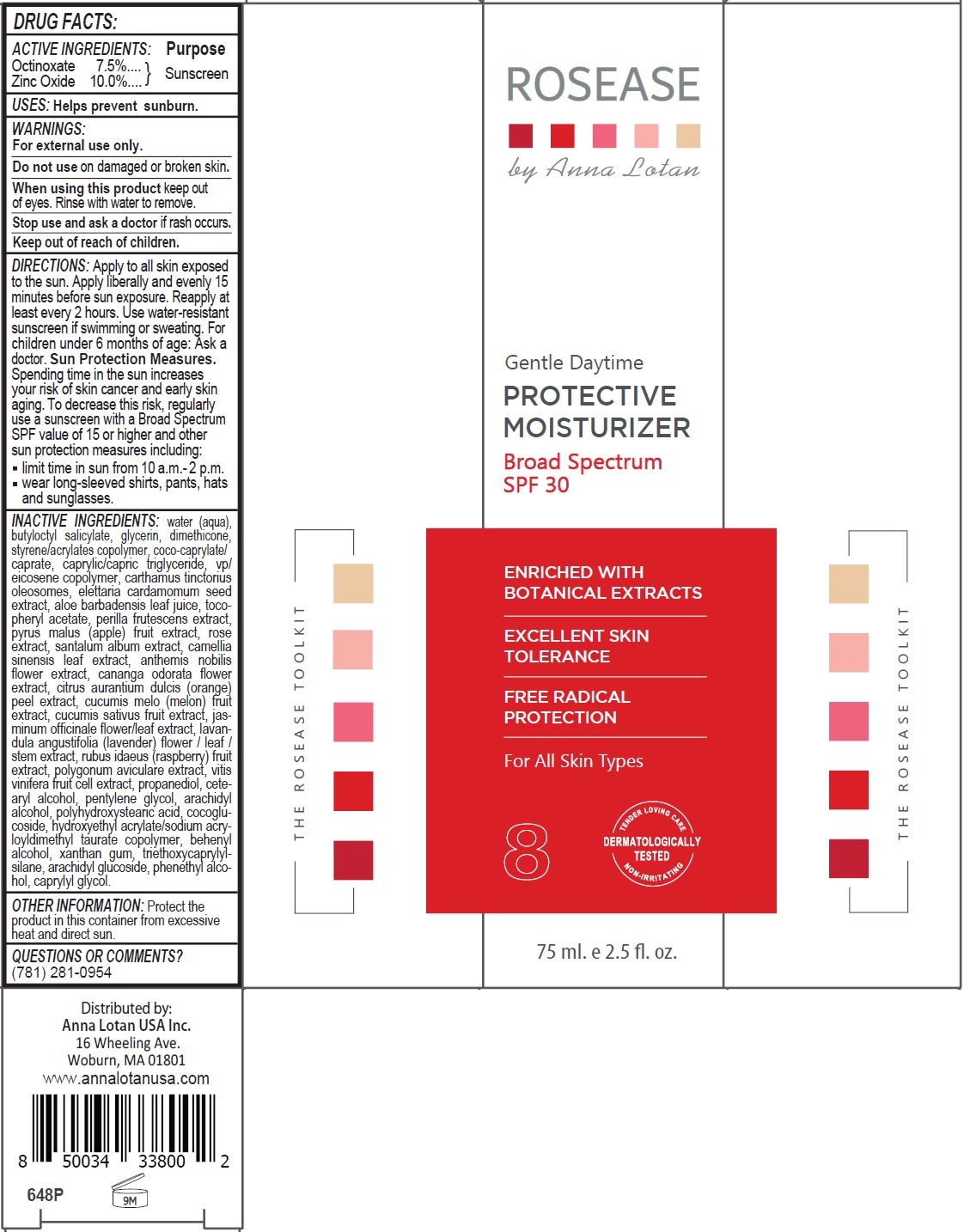 DRUG LABEL: Rosease By Anna Lotan Gentle Daytime Broad Spectrum SPF 30
NDC: 76446-648 | Form: CREAM
Manufacturer: Anna Lotan Ltd
Category: otc | Type: HUMAN OTC DRUG LABEL
Date: 20241004

ACTIVE INGREDIENTS: OCTINOXATE 7.5 g/100 mL; ZINC OXIDE 10 g/100 mL
INACTIVE INGREDIENTS: WATER; BUTYLOCTYL SALICYLATE; GLYCERIN; DIMETHICONE; STYRENE/ACRYLAMIDE COPOLYMER (500000 MW); COCOYL CAPRYLOCAPRATE; MEDIUM-CHAIN TRIGLYCERIDES; VINYLPYRROLIDONE/EICOSENE COPOLYMER; CARTHAMUS TINCTORIUS SEED OLEOSOMES; CARDAMOM; ALOE VERA LEAF; .ALPHA.-TOCOPHEROL ACETATE; PERILLA FRUTESCENS LEAF; APPLE; ROSA CENTIFOLIA FLOWER; SANDALWOOD; GREEN TEA LEAF; CHAMAEMELUM NOBILE FLOWER; CANANGA ODORATA FLOWER; ORANGE PEEL; MUSKMELON; CUCUMBER; JASMINUM OFFICINALE FLOWER; LAVANDULA ANGUSTIFOLIA SUBSP. ANGUSTIFOLIA FLOWERING TOP; RASPBERRY; POLYGONUM AVICULARE TOP; VITIS VINIFERA HIGH TANNIN CULTIVAR FRUIT CELL LYSATE; PROPANEDIOL; CETOSTEARYL ALCOHOL; PENTYLENE GLYCOL; ARACHIDYL ALCOHOL; POLYHYDROXYSTEARIC ACID (2300 MW); COCO GLUCOSIDE; HYDROXYETHYL ACRYLATE/SODIUM ACRYLOYLDIMETHYL TAURATE COPOLYMER (100000 MPA.S AT 1.5%); DOCOSANOL; XANTHAN GUM; TRIETHOXYCAPRYLYLSILANE; ARACHIDYL GLUCOSIDE; PHENYLETHYL ALCOHOL; CAPRYLYL GLYCOL

ROSEASE by Anna Lotan Gentle Daytime PROTECTIVE MOISTURIZER Broad Spectrum SPF 30

ACTIVE INGREDIENTS:

Octinoxate 7.5%
Zinc Oxide 10.0%

Purpose

Sunscreen

USES:

Helps prevent sunburn.

WARNINGS:

For external use only.

Do not use on damaged or broken skin.

When using this product keep out of eyes. Rinse with water to remove.

Stop use and ask a doctor if rash occurs.

Keep out of reach of children.

DIRECTIONS:

Apply to all skin exposed to the sun. Apply liberally and evenly 15 minutes before sun exposure. Reapply at least every 2 hours. Use water-resistant sunscreen if swimming or sweating. For children under 6 months of age: Ask a doctor. Sun Protection Measures. Spending time in the sun increases your risk of skin cancer and early skin aging. To decrease this risk, regularly use a sunscreen with a Broad Spectrum SPF value of 15 or higher and other sun protection measures including:
• limit time in sun from 10 a.m.- 2 p.m.
• wear long-sleeved shirts, pants, hats and sunglasses.

INACTIVE INGREDIENTS:

water (aqua), butyloctyl salicylate, glycerin, dimethicone, styrene/acrylates copolymer, coco-caprylate/caprate, caprylic/capric triglyceride, vp/eicosene copolymer, carthamus tinctorius oleosomes, elettaria cardamomum seed extract, aloe barbadensis leaf juice, tocopheryl acetate, perilla frutescens extract, pyrus malus (apple) fruit extract, rose extract, santalum album extract, camellia sinensis leaf extract, anthemis nobilis flower extract, cananga odorata flower extract, citrus aurantium dulcis (orange) peel extract, cucumis melo (melon) fruit extract, cucumis sativus fruit extract, jasminum officinale flower/leaf extract, lavandula angustifolia (lavender) flower / leaf / stem extract, rubus idaeus (raspberry) fruit extract, polygonum aviculare extract, vitis vinifera fruit cell extract, propanediol, cetearyl alcohol, pentylene glycol, arachidyl alcohol, polyhydroxystearic acid, cocoglucoside, hydroxyethyl acrylate/sodium acryloyldimethyl taurate copolymer, behenyl alcohol, xanthan gum, triethoxycaprylylsilane, arachidyl glucoside, phenethyl alcohol, caprylyl glycol.

OTHER INFORMATION:

Protect the product in this container from excessive heat and direct sun.

QUESTIONS OR COMMENTS?

(781) 281-0954

ENRICHED WITH BOTANICAL EXTRACTS

EXCELLENT SKIN TOLERANCE

FREE RADICAL PROTECTION

For All Skin Types

8

DERMATOLOGICALLY TESTED
TENDER LOVING CARE
NON-IRRITATING

THE ROSEASE TOOLKIT

Distributed by:
Anna Lotan USA Inc.
16 Wheeling Ave.
Woburn, MA 01801
www.annalotanusa.com